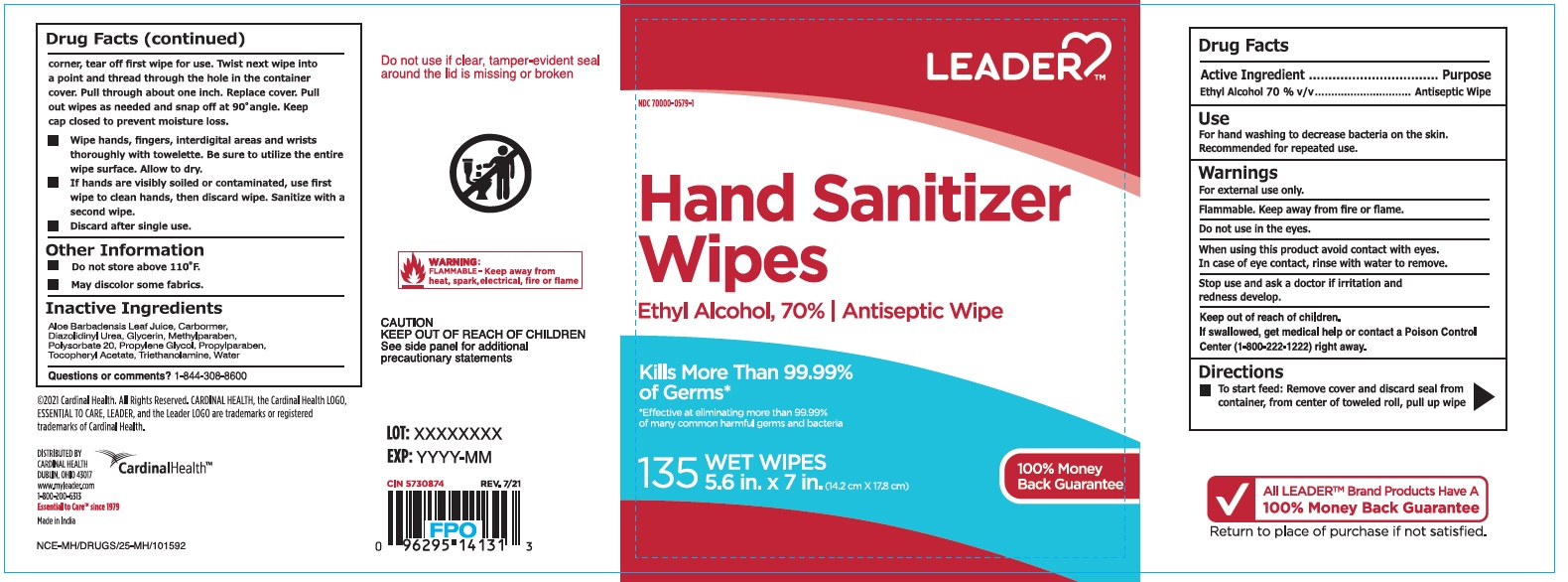 DRUG LABEL: Hand Sanitizer
NDC: 70000-0579 | Form: CLOTH
Manufacturer: Cardinal Health
Category: otc | Type: HUMAN OTC DRUG LABEL
Date: 20251023

ACTIVE INGREDIENTS: ALCOHOL 70 mL/100 mL
INACTIVE INGREDIENTS: ALOE VERA LEAF; POLYSORBATE 20; PROPYLPARABEN; WATER; DIAZOLIDINYL UREA; GLYCERIN; METHYLPARABEN; PROPYLENE GLYCOL; CARBOMER HOMOPOLYMER, UNSPECIFIED TYPE; TROLAMINE; .ALPHA.-TOCOPHEROL ACETATE

Leader Hand Sanitizing Wipes

Active Ingredient(s)

Ethyl Alcohol 70% v/v. Purpose: Antiseptic Wipe

Purpose

Antiseptic Wipe

Use

For hand washing to decrease bacteria on the skin. Recommended for repeated use.

Warnings

For external use only. Flammable. Keep away from heat or flame. Do not use in the eyes.

When using this product avoid contact with eyes. In case of eye contact, rinse with water to remove.

Keep out of reach of children. If swallowed, get medical help or contact a Poison Control Center (1-800-222-1222) right away.

Stop use and ask a doctor if irritation and redness develop.

Keep out of reach of children. If swallowed, get medical help or contact a Poison Control Center (1-800-222-1222) right away.

Directions

- To start feed: Remove cover and discard seal from container, from center fo toweled roll, pull up wipe corner, tear off first wipe for use. Twist next wipe into a point and thread through the hole in the container cover. Pull through about one inch, Replace cover. Pull out wipes as needed and snap off at a 90 degree angle. Keep cap closed to prevent moisture loss.
- Wipe hands, fingers, interdigital areas and wrists thoroughly with towelette. Be sure to utilize the entire wipe surface. Allow to dry.
- If hands are visibly soiled or contaminated, use first wipe to clean hands, then discard wipe. Sanitize with a second wipe.
- Discard after single use.

Other information

- Do not store above 110 degrees F

Inactive ingredients

Aloe Barbadensis Leaf Juice, Cabormer, Diazolidinyl Urea, Glycerin, Methylparaben, Polysorbate 20, Propylene Glycol, Propylparaben, Tocopheryl Acetate, Triethanolamine, Water